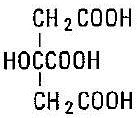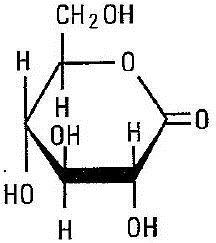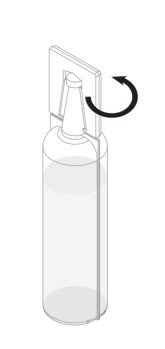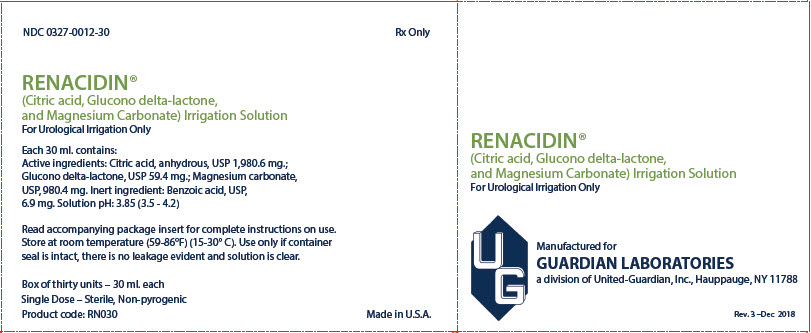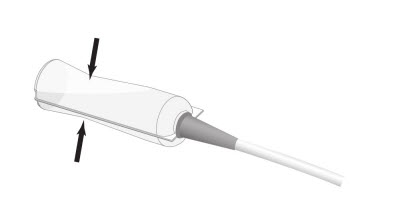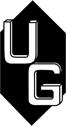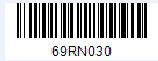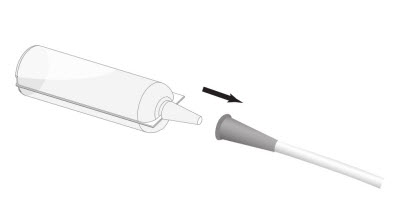 DRUG LABEL: Renacidin
NDC: 0327-0012 | Form: SOLUTION
Manufacturer: United-Guardian, Inc.
Category: prescription | Type: HUMAN PRESCRIPTION DRUG LABEL
Date: 20191217

ACTIVE INGREDIENTS: ANHYDROUS CITRIC ACID 6.602 g/100 mL; GLUCONOLACTONE 0.198 g/100 mL; MAGNESIUM CARBONATE 3.268 g/100 mL
INACTIVE INGREDIENTS: BENZOIC ACID

Renacidin® (Citric Acid, Glucono Delta-Lactone, and Magnesium Carbonate) Irrigation Solution

DESCRIPTION

Renacidin® (Citric Acid, Glucono delta-lactone, and Magnesium Carbonate) is a sterile, non-pyrogenic irrigation solution for use within the lower urinary tract in the dissolution of bladder calculi of the struvite or apatite variety, and prevention of encrustations of urethral catheters and cystostomy tubes.

Each 30 mL of Renacidin contains:

Active ingredients:
Citric Acid (anhydrous), USP 1980.6 mg
C6H8O7
Glucono delta-lactone, USP 59.4 mg
C6H10O6
Magnesium Carbonate, USP 980.4 mg
(MgCO3)4 · Mg(OH)2 · 5H2O

Citric Acid

Glucono delta-lactone

Magnesium Carbonate

(MgCO3)4 · Mg(OH)2 · 5H2O

Inert ingredients:
Benzoic Acid, USP 6.9 mg
Solution pH: 3.85 (3.5-4.2)

CLINICAL PHARMACOLOGY

Renacidin's action on susceptible apatite calculi results from an exchange of magnesium from the irrigating solution for calcium contained in the stone matrix. The magnesium salts thereby formed are soluble in the gluconocitrate irrigating solution resulting in the dissolution of the calculus. Struvite calculi are composed mainly of magnesium ammonium phosphates which are solubilized by Renacidin due to its acidic pH. Renacidin is not effective for dissolution of calcium oxalate, uric acid or cysteine stones.

INDICATIONS AND USAGE

Renacidin is indicated for dissolution of bladder calculi of the struvite or apatite variety by local intermittent irrigation through a urethral catheter or cystostomy tube as an alternative or adjunct to surgical procedures.

Renacidin is also indicated for use as an intermittent irrigating solution to prevent encrustations of indwelling urethral catheters and cystostomy tubes.

CONTRAINDICATIONS

Renacidin is contraindicated in the presence of demonstrable urinary tract extravasation.

WARNINGS

Renacidin use should be stopped immediately if the patient develops fever, urinary tract infection, signs and symptoms consistent with urinary tract infection, or persistent flank pain. Irrigation should be stopped if elevated serum creatinine develops.

The contents of individual Renacidin containers should not be combined for use as continuous irrigation of the urinary tract because of complications that may arise from inadequate aseptic technique. Terminal sterilization processes that are not adequate may result in sepsis and/or injury to product handlers (e.g., irritation to exposed, unprotected areas of the skin).

Serious adverse reactions, including sepsis and hypermagnesemia, have been reported to occur when Renacidin was used for continuous irrigation of the upper urinary tract. Renacidin is not indicated for continuous irrigation of the upper urinary tract.

PRECAUTIONS

Maintain Patency of the Urethral Catheter or Cystostomy Tube

Care must be taken during therapy with Renacidin to maintain the patency of the urethral catheter or cystostomy tube. Calculus fragments and debris may obstruct the catheter. Catheter outflow blockage may be prevented by flushing the catheter with saline and repositioning of the catheter. Frequent monitoring of the system should be performed by a nurse, an aide or any person with sufficient skills to be able to detect any problems with the patency of the catheter. At the first sign of obstruction, Renacidin should be discontinued.

Caution in Patients with Vesicoureteral Reflux

Patients with an indwelling urethral catheter or a cystostomy tube may have undiagnosed vesicoureteral reflux. Appropriate evaluation prior to initiation of Renacidin is recommended. If reflux is demonstrated, the potential benefits of therapy should outweigh the risks, and all recommended safety monitoring precautions should be strictly implemented.

Safety Monitoring While on Therapy with Renacidin

Patients should be monitored throughout the course of therapy with Renacidin. Serum creatinine, phosphate and magnesium should be obtained every several days. Urine specimens should be collected for culture and antibacterial sensitivity approximately every three days and at the first sign of fever. Therapy with Renacidin should be stopped if any culture exhibits growth and appropriate antibacterial therapy should be initiated. Therapy with Renacidin may be started again after a course of antibacterial therapy upon demonstration of sterile urine. Struvite calculi frequently contain bacteria within the stone and antibacterial therapy should therefore be continued throughout the course of dissolution therapy. An elevated serum creatinine concentration is also an indication to stop therapy with Renacidin.

Concomitant Use with Medications Containing Magnesium

Concomitant use of Renacidin and medications containing magnesium may contribute to hypermagnesemia in susceptible individuals, such as patients with vesicoureteral reflux. Renacidin Irrigation should be used with caution in patients taking concomitant medications containing magnesium.

Carcinogenesis, Mutagenesis, Impairment of Fertility

Long term studies to evaluate carcinogenic potential of Renacidin in animals have not been conducted. Mutagenicity studies have not been conducted.

Pregnancy Category C

Animal reproduction studies have not been conducted with Renacidin. It is also not known whether Renacidin can cause fetal harm when administered to a pregnant woman or can affect reproduction capacity. Renacidin should be given to a pregnant woman only if clearly needed.

Nursing Mothers

Magnesium is known to be excreted into human milk. It is not known whether Renacidin is excreted in human milk. Because many drugs are excreted in human milk, caution should be exercised when Renacidin is administered to a nursing woman.

ADVERSE REACTIONS

The most common adverse reactions with use of Renacidin for dissolution of bladder calculi or prevention of encrustations of indwelling urethral catheters are “bladder irritability” and chemical cystitis, both reported to occur in approximately 3% of patients. A transient burning sensation in the bladder following Renacidin has been reported to occur in less than 1% of patients receiving Renacidin.

DOSAGE AND ADMINISTRATION

Renacidin for local irrigation within the lower urinary tract is available in single-use 30 mL containers.

Prepare and Administer the Dose:

Step 1: Inspect Renacidin visually for particulate matter and discoloration prior to administration. If particulate matter or discoloration are observed, do not administer.

Step 2: Remove the plastic tab connected to the conical tip of the Renacidin container by twisting the plastic tab. See Figure 1.

Figure 1

Step 3: Connect the conical tip of the Renacidin container to the end of the urethral catheter or cystostomy tube. See Figure 2.

Figure 2

Step 4: Squeeze the Renacidin container to expel the entire contents into the urethral catheter or cystostomy tube. See Figure 3.

Figure 3

For Dissolution of Bladder Calculi: Instill 30 mL (one container) of Renacidin into the bladder via a urethral catheter or cystostomy tube. Clamp the urethral catheter or cystostomy tube for 30 to 60 minutes. Release the clamp and drain the bladder. Repeat the instillation procedure 4 to 6 times a day. Monitor for dissolution of calculi.

For Prevention of Encrustations in Urethral Catheters and Cystostomy Tubes: Instill 30 mL (one container) of Renacidin into the urethral catheter or cystostomy tube. Clamp the urethral catheter or cystostomy tube for 10 minutes. Remove the clamp and drain the bladder. Repeat the instillation procedure 3 times a day.

HOW SUPPLIED

Renacidin is available as a sterile, non-pyrogenic irrigation solution in 30 mL single-use, low density, polyethylene containers, supplied in boxes of 30 containers each. Exposure of Renacidin to heat or cold should be minimized. Renacidin should be stored at room temperature, 59° to 86°F (15° to 30°C). Avoid excessive heat or cold (keep from freezing). Brief exposure to temperatures of up to 40°C or temperatures down to 5°C does not adversely affect the product.

NDC: 0327-0012-30

PRODUCT CODE: RN030

Revised: December, 2018

Manufactured for
GUARDIAN LABORATORIES
A DIVISION OF
UNITED-GUARDIAN, INC.
Hauppauge, N.Y. 11788

PACKAGE/LABEL PRINCIPAL DISPLAY PANEL

Carton Label

NDC 0327-0012-30 Rx Only

RENACIDIN®
(Citric acid, Glucono delta-lactone,
and Magnesium Carbonate) Irrigation Solution
For Urological Irrigation Only

Each 30 ml. contains:
Active ingredients: Citric acid, anhydrous, USP 1,980.6 mg.;
Glucono delta-lactone, USP 59.4 mg.; Magnesium carbonate,
USP, 980.4 mg. Inert ingredient: Benzoic acid, USP,
6.9 mg. Solution pH: 3.85 (3.5 - 4.2)

Read accompanying package insert for complete instructions on use.
Store at room temperature (59-86°F) (15-30°C). Use only if container
seal is intact, there is no leakage evident and solution is clear.

Box of thirty units – 30 ml. each
Single Dose – Sterile, Non-pyrogenic
Product code: RN030

Made in U.S.A.

RENACIDIN®
(Citric acid, Glucono delta-lactone,
and Magnesium Carbonate) Irrigation Solution
For Urological Irrigation Only

Manufactured for

GUARDIAN LABORATORIES
a division of United-Guardian, Inc., Hauppauge, NY 11788

Rev. 3 - Dec 2018